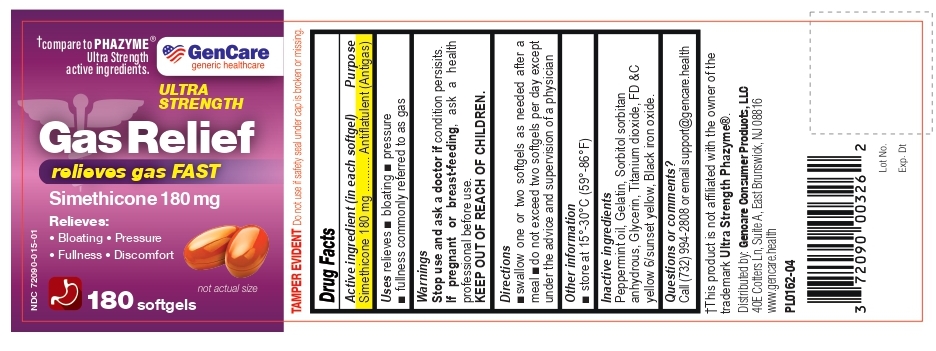 DRUG LABEL: Gas Relief
NDC: 72090-015 | Form: CAPSULE, LIQUID FILLED
Manufacturer: Pioneer Life Sciences, LLC
Category: otc | Type: HUMAN OTC DRUG LABEL
Date: 20260213

ACTIVE INGREDIENTS: DIMETHICONE 180 mg/1 1
INACTIVE INGREDIENTS: PEPPERMINT OIL; Gelatin; SORBITOL; Glycerin; Titanium dioxide; FD&C YELLOW NO. 6; FERROSOFERRIC OXIDE

Gas Relief Simethicone 180 mg Softgels

Active ingredient (in each softgel)

Simethicone 180 mg

Purpose

Antiflatulent (Antigas)

Use

relieves ■ bloating ■ pressure ■ fullness commonly referred to as gas

Warnings

Stop use and ask a doctor if condition persisits.

If pregnant or breast-feeding, ask a health Professional before use .

KEEP OUT OF REACH OF CHILDREN.

Directions

■swallow one or two softgels as needed after a meal

■do not exceed two softgels per day except under the advice and supervision of a physician

Other Information

- store at 15 to 30ºC (59 to 86ºF)

Inactive Ingredients

Peppermint oil, Gelatin, Sorbitol sorbitan anhydrous, Glycerin, Titanium dioxide, FD &C yellow 6/sunset yellow, Black iron oxide.

Questions or Comments?

Call (732) 994-2808 or email support@gencare.health